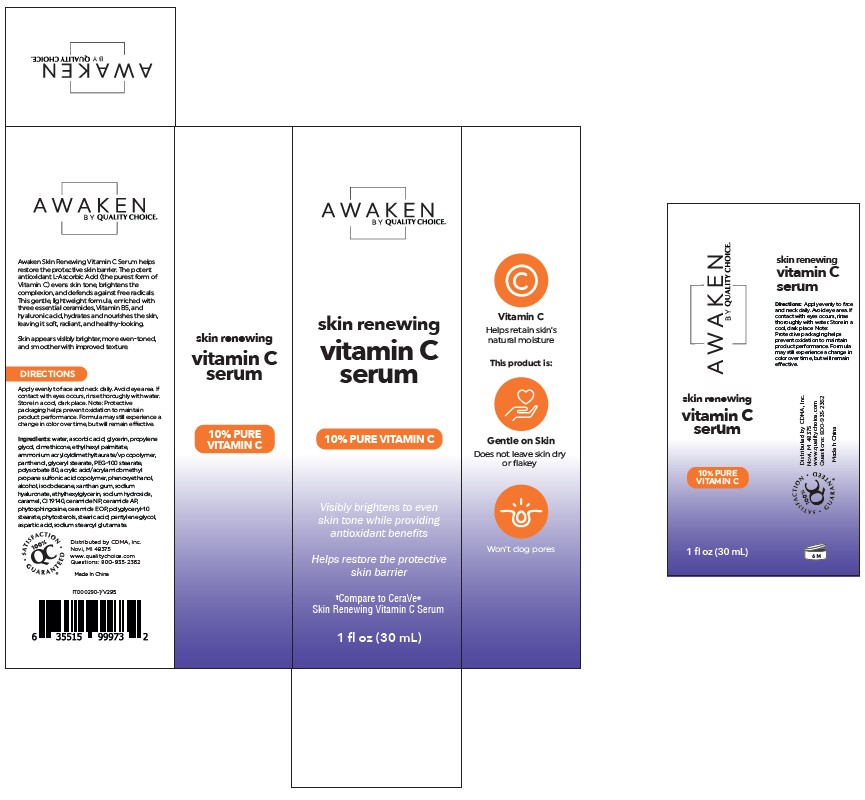 DRUG LABEL: Skin Renewing Serum
NDC: 75376-102 | Form: CREAM
Manufacturer: Guangzhou Danting Bath&Body Care Industry Co. Ltd
Category: otc | Type: HUMAN OTC DRUG LABEL
Date: 20250823

ACTIVE INGREDIENTS: ASCORBIC ACID 100 mg/1 mL
INACTIVE INGREDIENTS: WATER; GLYCERIN; PROPYLENE GLYCOL; DIMETHICONE; ETHYLHEXYL PALMITATE; AMMONIUM ACRYLOYLDIMETHYLTAURATE/VP COPOLYMER; PANTHENOL; GLYCERYL STEARATE; PEG-100 STEARATE; POLYSORBATE 80; PHENOXYETHANOL; ALCOHOL; ISODODECANE; XANTHAN GUM; SODIUM HYDROXIDE; CARAMEL; CI 19140; CERAMIDE NP; CERAMIDE AP; PHYTOSPHINGOSINE; CERAMIDE 1; POLYGLYCERYL-10 STEARATE; STEARIC ACID; PENTYLENE GLYCOL; ASPARTIC ACID; SODIUM STEAROYL GLUTAMATE

QC Foaming Facial Cleanser

Active Ingredient

Ascorbic Acid 10%

Purpose

Moisturizer

DOSAGE AND ADMINISTRATION

To brighten skin, hydrate, and moisturize

WARNINGS

If contact with eyes occurs, rinse thoroughly with water.

WHEN USING

Avoid eye area

INDICATIONS AND USAGE

Apply evenly to face and neck daily.

STORAGE AND HANDLING

Store in a cool, dark place

Note: Protective
packaging helps prevent oxidation to maintain
product performance. Formula may still experience a
change in color over time, but will remain effective.